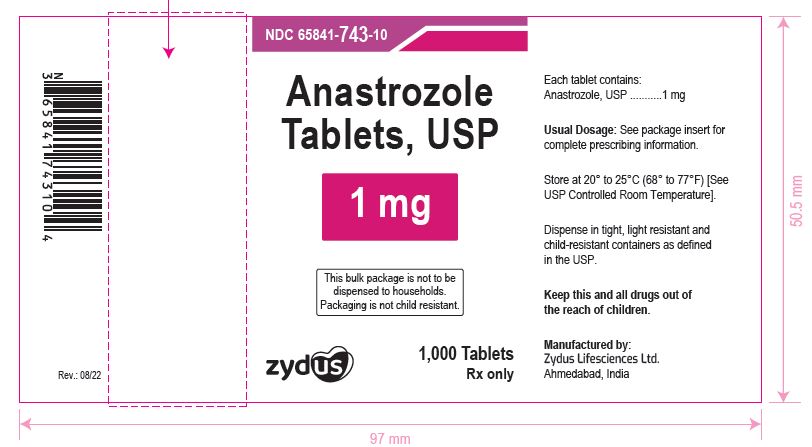 DRUG LABEL: Anastrozole
NDC: 65841-743 | Form: TABLET, COATED
Manufacturer: Zydus Lifesciences Limited
Category: prescription | Type: HUMAN PRESCRIPTION DRUG LABEL
Date: 20241125

ACTIVE INGREDIENTS: ANASTROZOLE 1 mg/1 1
INACTIVE INGREDIENTS: HYPROMELLOSES; LACTOSE MONOHYDRATE; MAGNESIUM STEARATE; SODIUM STARCH GLYCOLATE TYPE A POTATO; POVIDONE; TITANIUM DIOXIDE; POLYETHYLENE GLYCOL, UNSPECIFIED

ANASTROZOLE TABLETS

PACKAGE LABEL.PRINCIPAL DISPLAY PANEL

Anastrozole Tablets, 1 mg

NDC 65841-743-10

1,000 tablets

Rx only